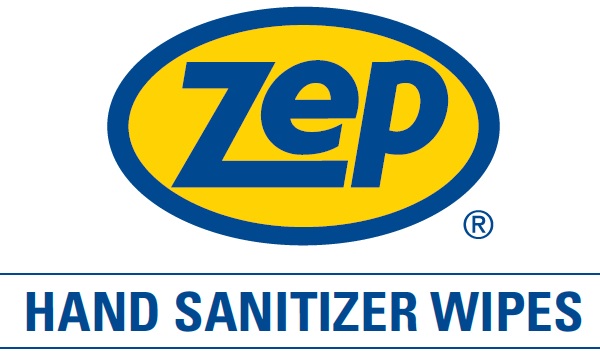 DRUG LABEL: Zep Hand Sanitizer Wipes
NDC: 66949-405 | Form: SWAB
Manufacturer: Zep Inc.
Category: otc | Type: HUMAN OTC DRUG LABEL
Date: 20251226

ACTIVE INGREDIENTS: ALCOHOL 70 mL/1 1
INACTIVE INGREDIENTS: ISOPROPYL MYRISTATE; ALOE VERA LEAF; METHYL SALICYLATE; .ALPHA.-TOCOPHEROL; PROPYLENE GLYCOL; UNDECETH-7; WATER

66949-405 / 1405 Hand Sanitizer Wipes

Active Ingredient

Ethyl Alcohol 70%

Purpose

Antiseptic

Uses

- For handwashing to decrease bacteria on the skin.
- After changing diapers.
- After assisting ill persons.
- Before contact with a person under medical care or treatment.
- Recommended for repeat use.

Warnings

Flammable. Keep away from fire or flame.

For external use only.

Do not use in the eyes.

When using this product do not get into eyes. If contact occurs, rinse thoroughly with water.

Stop using and ask a doctor

Stop use and ask a doctor if irritation and redness develop. If condition persists for more than 72 hours consult a doctor.

Keep out of reach of children. If swallowed, get medical help or contact a Poison Control Center right away.

Directions

- Wet hands thoroughly with product and allow to dry.
- Children under six years of age should be supervised when using this product.

Other Information

- Store below 110°F (43°C).

Inactive Ingredients

Water, Propylene Glycol, Undeceth-7, Isopropyl Myristate, Aloe Barbadensis Leaf Juice, Methyl Salicylate, Tocopherol Acetate (Vitamin E)